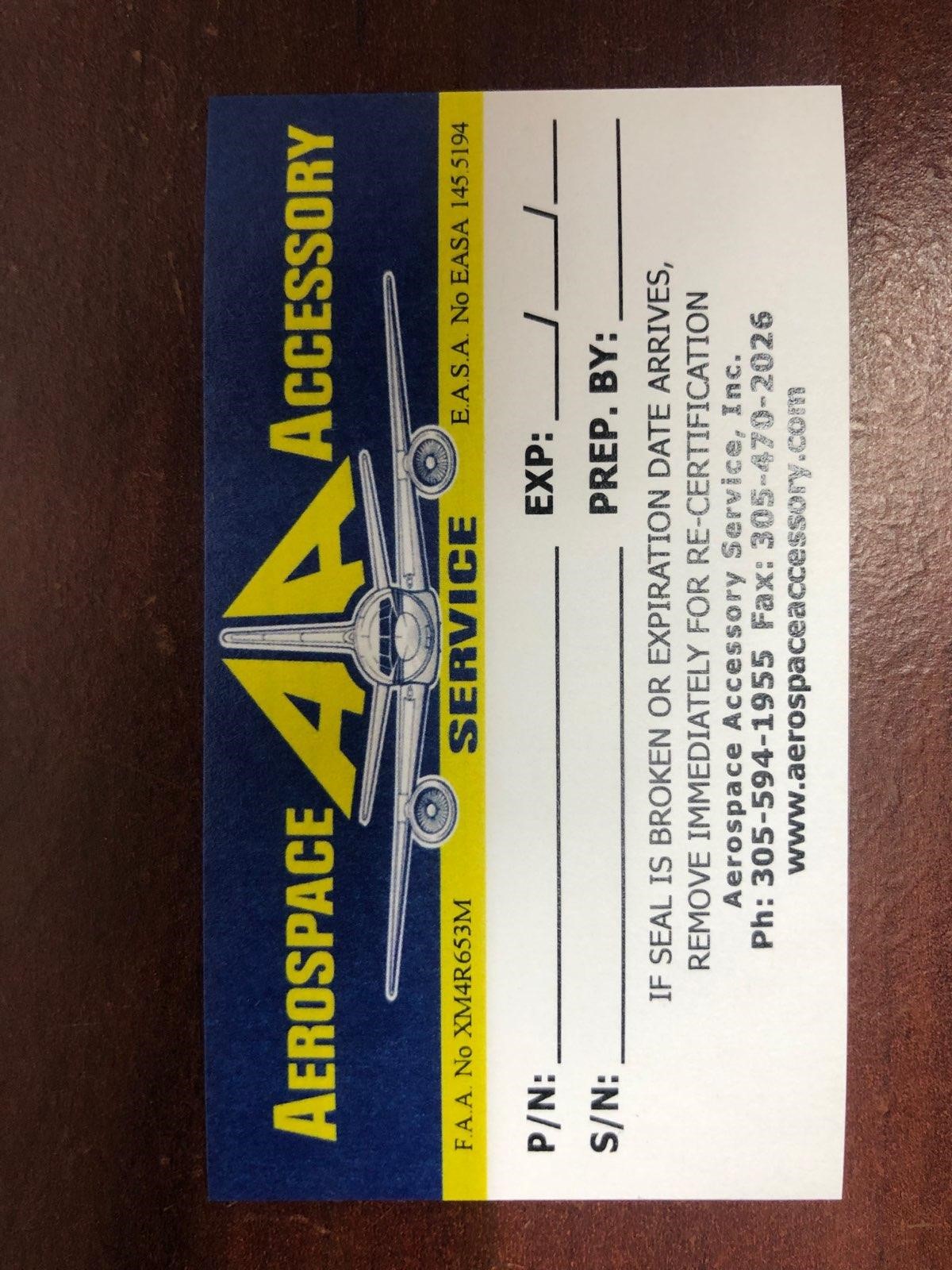 DRUG LABEL: Model AA1620 FJA
NDC: 27860-004 | Form: KIT | Route: TOPICAL
Manufacturer: Aerospace Accessory Service, Inc
Category: other | Type: MEDICAL DEVICE
Date: 20210107

ACTIVE INGREDIENTS: POVIDONE-IODINE 10 mg/1 mL
INACTIVE INGREDIENTS: CITRIC ACID MONOHYDRATE; SODIUM PHOSPHATE, DIBASIC, ANHYDROUS; NONOXYNOL-9; SODIUM HYDROXIDE; WATER

Model AA 1620FJA

Aerospace Accessory Service

P/N:

S/N:

EXP:

Prep. By: